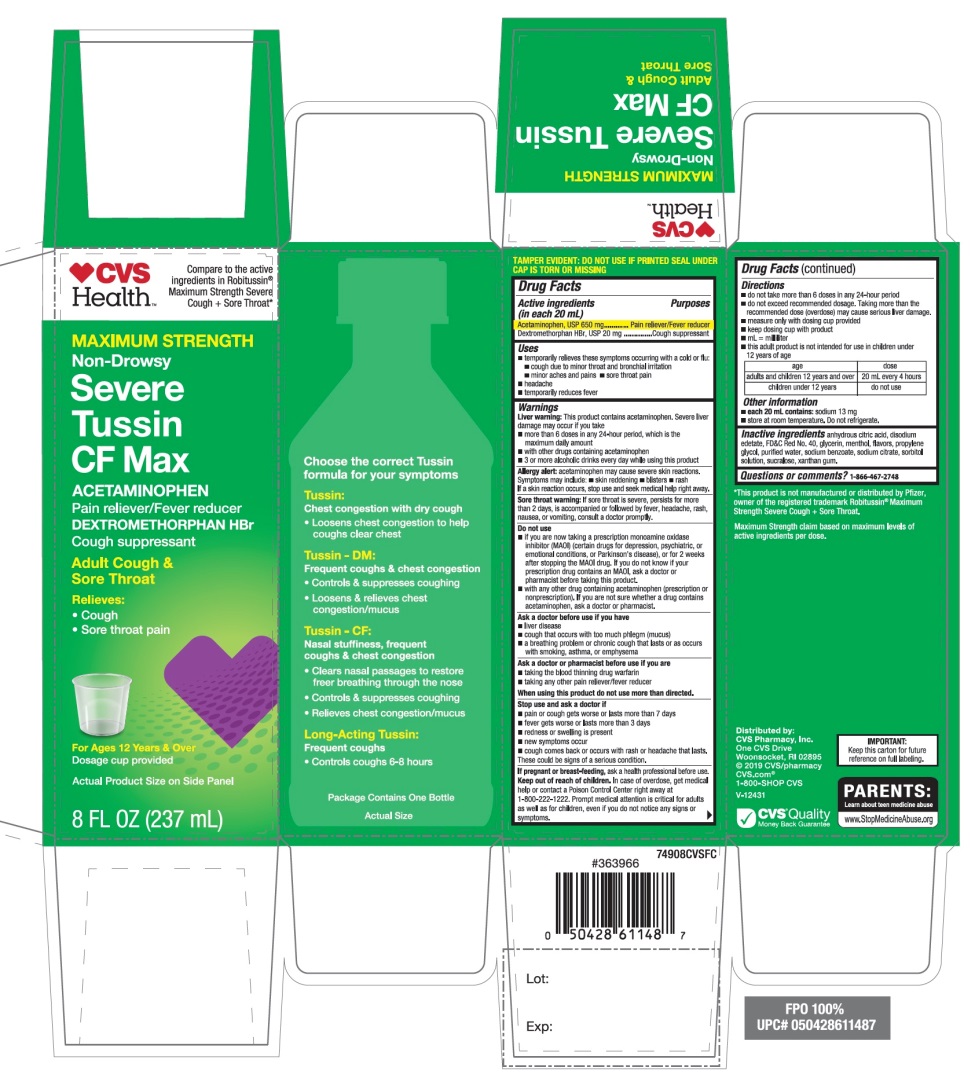 DRUG LABEL: CVS Severe Tussin CF Max
NDC: 69842-947 | Form: SOLUTION
Manufacturer: CVS PHARMACY
Category: otc | Type: HUMAN OTC DRUG LABEL
Date: 20251210

ACTIVE INGREDIENTS: ACETAMINOPHEN 650 mg/20 mL; DEXTROMETHORPHAN HYDROBROMIDE 20 mg/20 mL
INACTIVE INGREDIENTS: ANHYDROUS CITRIC ACID; EDETATE DISODIUM; FD&C RED NO. 40; GLYCERIN; MENTHOL, UNSPECIFIED FORM; PROPYLENE GLYCOL; WATER; SODIUM BENZOATE; SODIUM CITRATE, UNSPECIFIED FORM; SORBITOL; SUCRALOSE; XANTHAN GUM

CVS Health™Maximum Strength Severe Tussin CF Max Drug Facts

Active ingredients (in each 20 mL)

Acetaminophen, USP 650 mg

Dextromethorphan HBr, USP 20 mg

Purposes

Pain reliever/fever reducer

Cough suppressant

Uses

- temporarily relieves these symptoms occurring with a cold or flu:
- cough due to minor throat and bronchial irritation
- minor aches and pains
- sore throat
- headache
- temporarily reduces fever

Warnings

Liver warning: This product contains acetaminophen. Severe liver damage may occur if you take

- more than 6 doses in any 24 hours period, which is the maximum daily amount
- with other drugs containing acetaminophen
- 3 or more alcoholic drinks every day while using this product

Allergy alert:Acetaminophen may cause severe skin reactions. Symptoms may include:

- skin reddening
- blisters
- rash

If a skin reaction occurs, stop use and seek medical help right away.

Sore throat warning:If sore throat is severe, persists for more than 2 days, is accompanied or followed by fever, headache, rash, nausea, or vomiting, consult a doctor promptly.

Do not use

- if you are now taking a prescription monoamine oxidase inhibitor (MAOI) (certain drugs for depression, psychiatric, or emotional conditions, or Parkinson’s disease), or for 2 weeks after stopping the MAOI drug. If you do not know if your prescription drug contains an MAOI, ask a doctor or pharmacist before taking this product.
- with any other drug containing acetaminophen (prescription or nonprescription). If you are not sure whether a drug contains acetaminophen, ask a doctor or pharmacist.

Ask a doctor before use if you have

- liver disease
- cough that occurs with too much phlegm (mucus)
- a breathing problem or chronic cough that lasts or as occurs with smoking, asthma or emphysema

Ask a doctor or pharmacist before use if you are

- taking the blood thinning drug warfarin
- Taking any other pain reliever/fever reducer

Stop use and ask a doctor if

- pain, cough, or nasal congestion gets worse or lasts more than 7 days
- fever gets worse or lasts more than 3 days
- redness or swelling is present
- new symptoms occur
- cough comes back or occurs with rash or headache that lasts. These could be signs of a serious condition.

If pregnant or breast-feeding,

ask a health professional before use.

Keep out of reach of children.

Overdose warning:In case of overdose, get medical help or contact a Poison Control Center right away (1-800-222-1222). Prompt medical attention is critical for adults as well as for children even if you do not notice any signs or symptoms.

Directions

- do not take more than 6 doses in any 24-hour period
- do not exceed recommended dosage. Taking more than the recommended dose (overdose) may cause serious liver damage.
- measure only with dosing cup provided
- keep dosing cup with product
- mL = milliliter
- this adult product is not intended for use in children under 12 years of age

Age | dose
adults and children; 12 years and over | 20 mL every 4 hours
children under 12 years | do not use

Other information

- each 20 mL contains:sodium 13 mg
- store at room temperature Do not refrigerate.

Inactive ingredients

anhydrous citric acid, edetate disodium, FD&C red #40, glycerin, menthol, flavors, propylene glycol, purified water, sodium benzoate, sodium citrate, sorbitol solution, sucralose, xanthan gum.

Questions or comments?

1-866-467-2748

Principal Display Panel

Compare to active ingredients in Robitussin®Maximum Strength Severe Cough + Sore Throat*

NDC# 69842-947-08

MAXIMUM STRENGTH

Non–Drowsy

Severe Tussin CF Max

ACETAMINOPHEN

Pain reliever / Fever reducer

DEXTROMETHORPHAN HBr

Cough Suppressant

Adult Cough & Sore Throat

Relieves:

- Cough
- Sore throat pain

For Ages 12 Years & older

Dosage cup provided

Actual Product Size on Side Panel

8 FL OZ (237 mL)

*This product is not manufactured or distributed by Pfizer, owner of the registered trademark Robitussin Maximum Strength Severe Cough + Sore Throat.

Maximum Strength claim based on maximum levels of active ingredients per dose.

IMPORTANT: Keep this carton for future reference on full labeling.

Distributed by:

CVS Pharmacy, Inc.

One CVS Drive

Woonsocket, RI 02895

© 2019 CVS/pharmacy

CVS.com

1-800-SHOP CVS

V-12431

CVS Quality

Money Back Guarantee